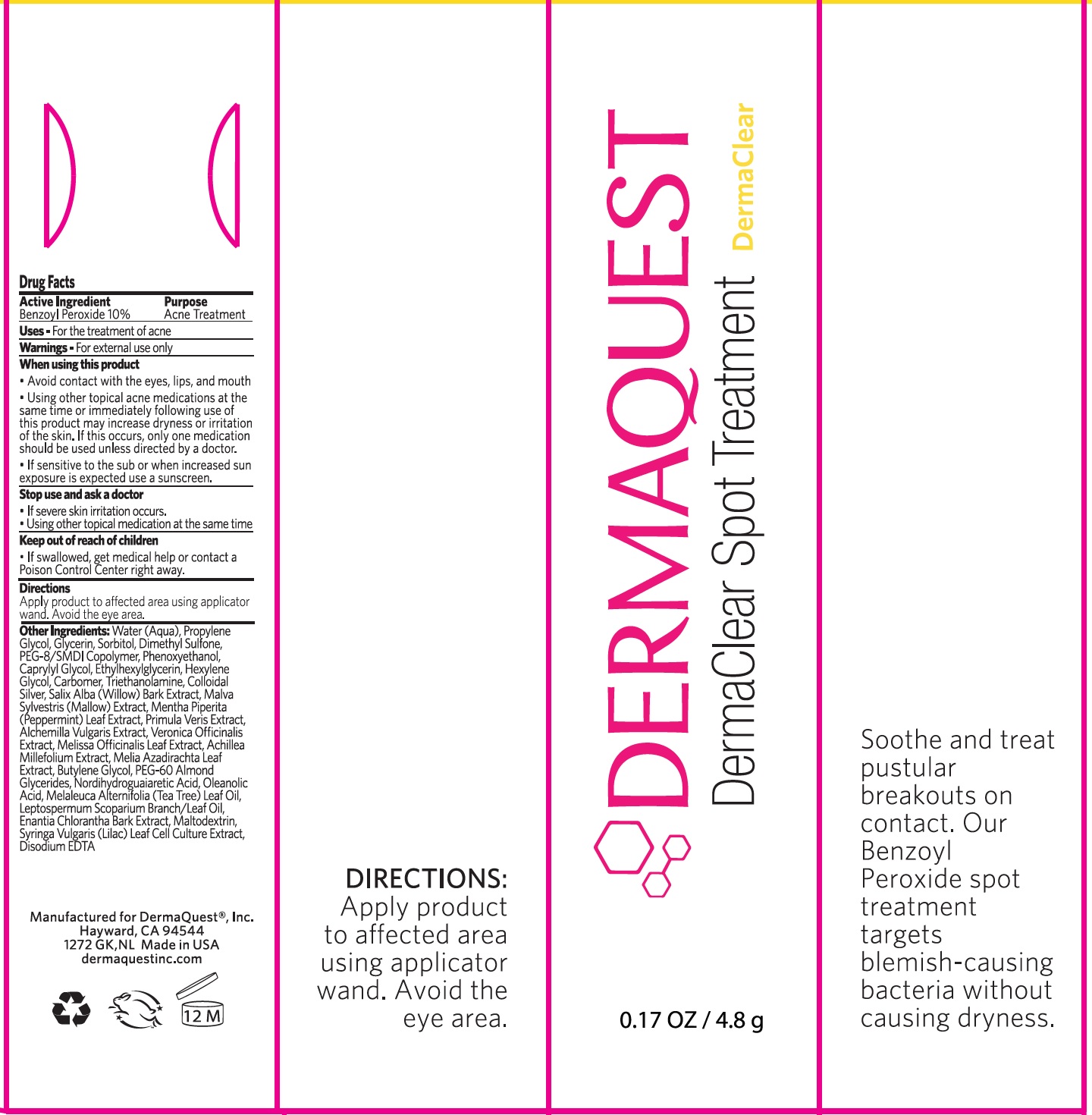 DRUG LABEL: Dermaclear Spot Treatment
NDC: 62742-4075 | Form: CREAM
Manufacturer: Allure Labs Inc
Category: otc | Type: HUMAN OTC DRUG LABEL
Date: 20241205

ACTIVE INGREDIENTS: BENZOYL PEROXIDE 100 mg/1 g
INACTIVE INGREDIENTS: HEXYLENE GLYCOL; PHENOXYETHANOL; CAPRYLYL GLYCOL; PROPYLENE GLYCOL; GLYCERIN; ALCHEMILLA XANTHOCHLORA FLOWERING TOP; VERONICA OFFICINALIS FLOWERING TOP; ACHILLEA MILLEFOLIUM; AZADIRACHTA INDICA LEAF; PEG-60 ALMOND GLYCERIDES; MASOPROCOL; TEA TREE OIL; MANUKA OIL; ANNICKIA CHLORANTHA BARK; DIMETHYL SULFONE; MALVA SYLVESTRIS FLOWERING TOP; MELISSA OFFICINALIS LEAF; BUTYLENE GLYCOL; OLEANOLIC ACID; WATER; SORBITOL; PEG-8/SMDI COPOLYMER; ETHYLHEXYLGLYCERIN; CARBOMER HOMOPOLYMER, UNSPECIFIED TYPE; TROLAMINE; SILVER; SALIX ALBA BARK; MALTODEXTRIN; MENTHA PIPERITA LEAF; PRIMULA VERIS; SYRINGA VULGARIS WHOLE; EDETATE DISODIUM

Drug Facts

Active Ingredient - Benzoyl Peroxide 10%

Purpose: Acne Treatment

Uses:

- For the treatment of acne

Warnings:

- For external use only

When using this product:

- Avoid contact with the eyes, lips, and mouth
- Using other topical acne medications at the same time or immediately following use of this product may increase dryness or irritation of the skin. If this occurs, only one medication should be used unless directed by a doctor.
- If sensitive to the sun or when increased sun exposure is expected use a sunscreen.

Stop use and ask a doctor:

- If severe skin irritation occurs.
- Using other topical medication at the same time

Keep out of reach of children:

If swallowed, get medical help or contact a Poison Control Centre right away.

Directions:

- Apply product to affected area using applicator wand. Avoid eye area.

Inactive Ingredients:

Water (Aqua),Propylene Glycol, Glycerin, Sorbitol, Dimethyl Sulfone, PEG-8/SMDI Copolymer, Phenoxyethanol, Caprylyl Glycol, Ethylhexylglycerin, Hexylene Glycol, Carbomer, Triethanolamine, Collidal Silver, Salix Alba (Willow) Bark Extract, Malva Sylvestns (Mallow) Extract, Mentha Pipenta (Peppermint) Leaf Extract, Primula Veris Extract, Alchemilla Vulgaris Extract, Veronica Officinalis Extract, Melissa Officinalis Leaf Extract, Achillea Millefolium Extract, Melia Azadirachta Leaf Extract, Butylene Glycol, PEG-60 Almond Glycerides, Nordihydroguaiaretic Acid, Oleanolic Acid, Melaleuca Alternifolia (Tea Tree) Leaf Oil, Leptospermum Scoparium Branch/ Leaf Oil, Enantia Chlorantha Bark Extract, Maltodextrin, Syringa Vulgaris (Lilac) Leaf Cell Culture Extract, Disodium EDTA

PACKAGE LABEL

Manufactured for DermaQuest®, Inc.

Hayward, CA 94544

1272 GK, NL Made in USA

dermaquestinc.com